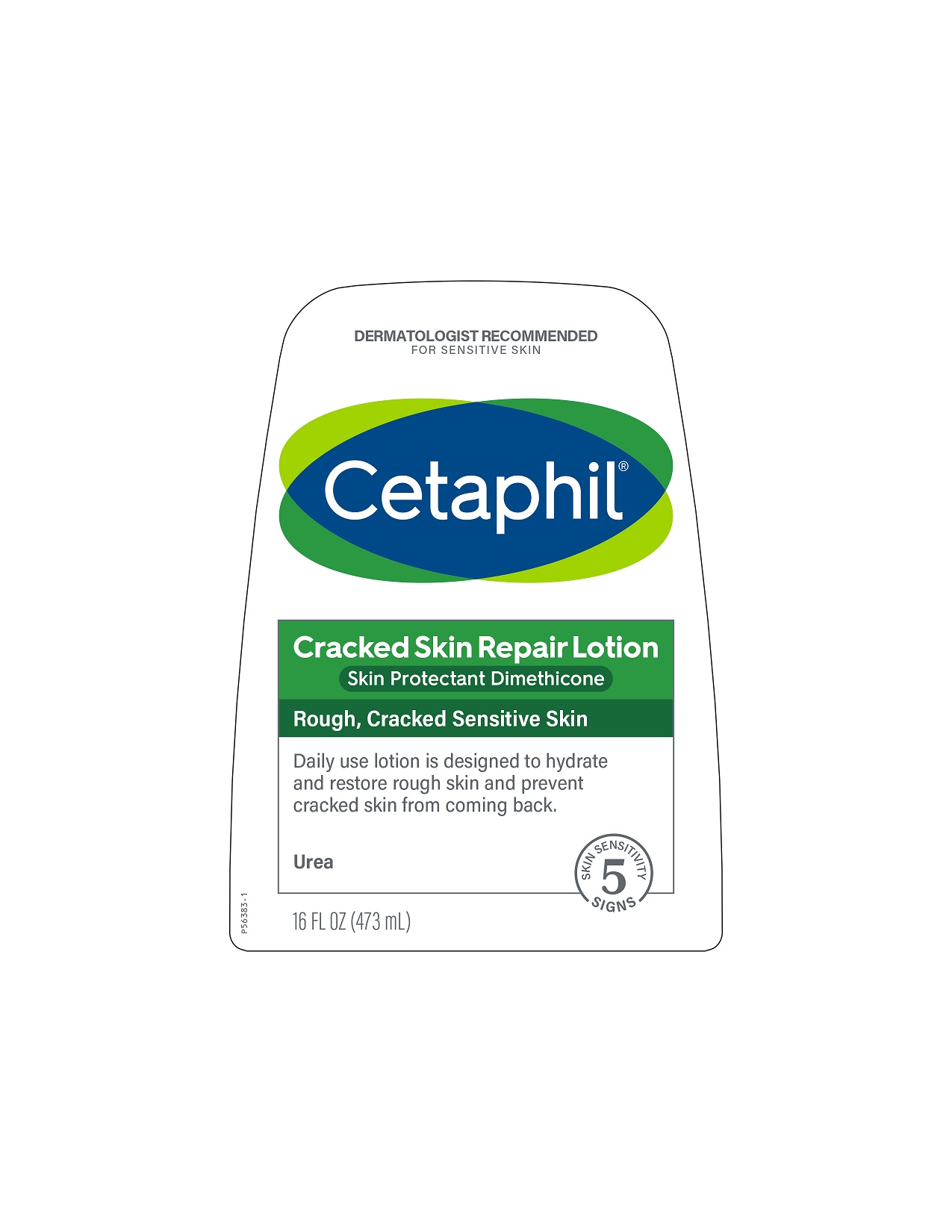 DRUG LABEL: Cetaphil Cracked Skin Repair
NDC: 0299-4114 | Form: LOTION
Manufacturer: Galderma Laboratories, L.P.
Category: otc | Type: HUMAN OTC DRUG LABEL
Date: 20231130

ACTIVE INGREDIENTS: Dimethicone 20 mg/1 mL
INACTIVE INGREDIENTS: Medium-Chain Triglycerides; Hydrogenated Castor Oil; Lactic Acid, Unspecified Form; Methoxy Peg-22/Dodecyl Glycol Copolymer; Methylparaben; Mineral Oil; Ceresin; Peg-7 Hydrogenated Castor Oil; Propylparaben; Sodium Lactate; Sorbitan Isostearate; Urea; Water

Drug Facts

Active ingredients......Purpose

Dimethicone 2%......Skin protectant

Uses

● helps prevent and temporarily protects and helps relieve chafed, chapped or cracked skin
● temporary protects minor:
● cuts ● scrapes ● burns
● helps prevent and protect from the drying effects of wind and cold weather

Warnings

For external use only.

When using this product ● do not get into eyes.

Stop use and ask a doctor if ● condition worsens ● symptoms last more than 7 days or clear up and occur again within a few days.

Do not use on ● deep or puncture wounds ● animal bites ● serious burns

Keep out of reach of children. If swallowed, get medical help or contact a Poison Control Center right away.

Directions

● Apply generously to affected area as needed

Inactive Ingredients

CAPRYLIC/CAPRIC TRIGLYCERIDE, HYDROGENATED CASTOR OIL, LACTIC ACID, METHOXY PEG-22/DODECYL GLYCOL COPOLYMER, METHYLPARABEN, MINERAL OIL, OZOKERITE, PEG-2 HYDROGENATED CASTOR OIL, PEG-7 HYDROGENATED CASTOR OIL, PROPYLPARABEN, SODIUM LACTATE, SORBITAN ISOSTEARATE, UREA, WATER

Questions or comments?

1-866-735-4137

Distributed By:
Galderma Laboratories, L.P.
Dallas, TX 75201

All trademarks are the property of their respective owners.

Made in Canada

cetaphil.com

PRINCIPLE DISPLAY PANEL - 16 FL OZ pump label

Dermatologist Recommended
For Sensitive Skin
Cetaphil®

Cracked Skin Repair Lotion
Skin Protectant Dimethicone

Rough, Cracked Sensitive Skin

Daily use lotion is designed to hydrate
and restore rough skin and prevent
cracked skin from coming back.
Urea

5 skin sensitivity signs

16 FL OZ (473 mL)
P56383-1